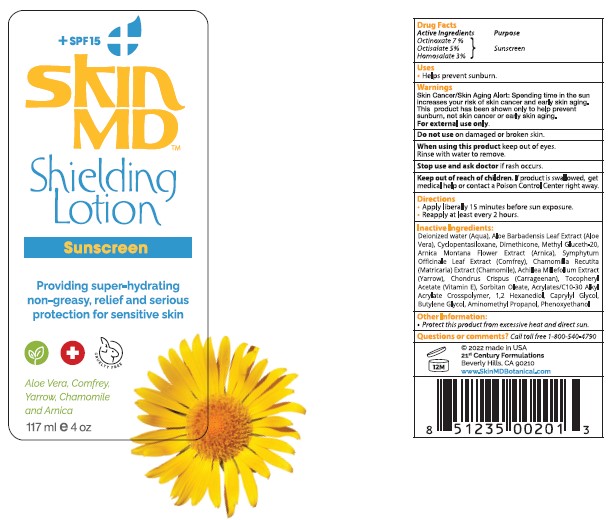 DRUG LABEL: skin MD
NDC: 44099-011 | Form: LOTION
Manufacturer: 21st Century Formulations
Category: otc | Type: HUMAN OTC DRUG LABEL
Date: 20251113

ACTIVE INGREDIENTS: OCTINOXATE 7 mg/100 mL; OCTISALATE 5 mg/100 mL; HOMOSALATE 3 mg/100 mL
INACTIVE INGREDIENTS: CYCLOMETHICONE 5; DIMETHICONE; METHYL GLUCETH-20; ARNICA MONTANA FLOWER; COMFREY LEAF; CHAMOMILE; ACHILLEA MILLEFOLIUM; CHONDRUS CRISPUS; .ALPHA.-TOCOPHEROL ACETATE; SORBITAN MONOOLEATE; 1,2-HEXANEDIOL; CAPRYLYL GLYCOL; BUTYLENE GLYCOL; AMINOMETHYLPROPANOL; PHENOXYETHANOL; CARBOMER COPOLYMER TYPE A (ALLYL PENTAERYTHRITOL CROSSLINKED); DIMETHICONE/VINYL DIMETHICONE CROSSPOLYMER (SOFT PARTICLE); BIS-HYDROXYETHOXYPROPYL DIMETHICONE (37 CST); ALOE VERA LEAF

21st Century Formulations - Skin MD Shielding Lotion (44099-011) DELIST 03, 04 & 05.

Active ingredients

Octinoxate 7%

Octisalate 5%

Homosalate 3%

Purpose

Sunscreen

Uses

- Helps prevent sunburn.
- Decreases the risk of skin cancer and early aging caused by the sun.

Warnings

For external use only.

Do not use

on damaged or broken skin

Stop use and ask a Doctor

if rash occurs.

When using this product

keep out of eyes. Rinse with water to remove.

Keep out of reach of children.

If product is swallowed, get medical help or contact a Poison Control Center right away.

Directions

- Apply liberally 15 minutes before sun exposure.
- Reapply at least every 2 hours.
  Spending time in the sun increases your risk of skin cancer and early skin aging.

Other information

- Protect this product from excessive heat and direct sun.

Inactive ingredients

Water (aqua), Aloe Barbadensis Leaf Extract (Aloe Vera), Cyclopentasiloxane, Dimethicone, Methyl Gluceth-20, Extracts of Arnica Montana Flower (Arnica), Symphytum Officinale Leaf (Camfrey), Chamomilla Recutita (Matricaria Chamomile), Achillea Millefolium (Yarrow), Chondrus Crispus (Carrageenan), Tocopheryl Acetate (Vitamin E), Sorbitan Oleate, 1,2 Hexanediol, Caprylyl Gylcol, Butylene Glycol, Aminomethyl Propanol, Phenoxyethanol (preservative), Acrylates/C10-30 Alkyl Acrylate Crosspolymer, Dimethicone/Vinyl Dimethicone Crosspolymer, Bis-Hydroxyethoxypropyl Dimethicone.

Questions?

Call toll free 1-800-540-4790

®2013 Made in USA

21st Century Formulations

Beverly Hills, CA 90210

www.skinmdnatural.com